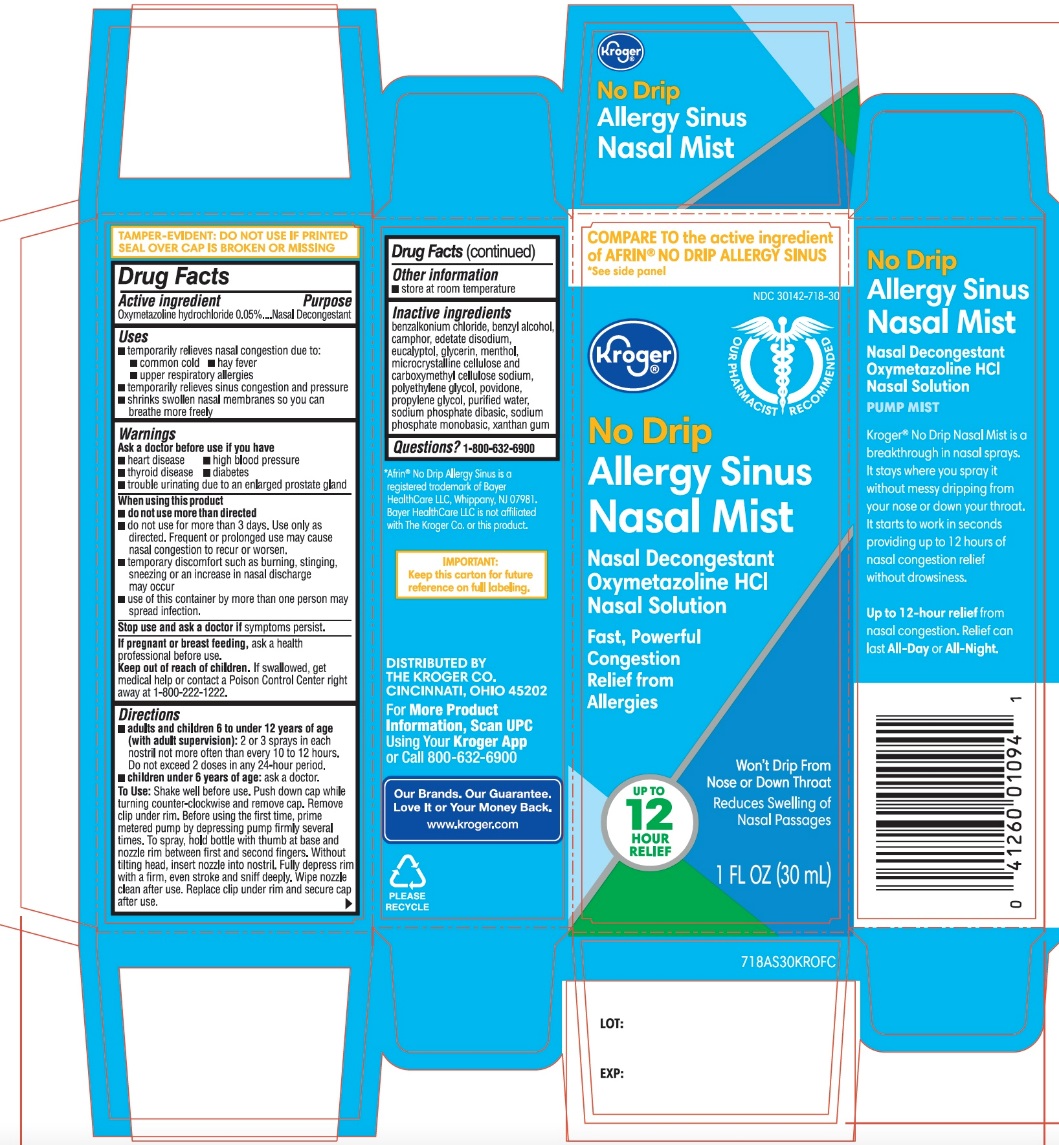 DRUG LABEL: Kroger

NDC: 30142-718 | Form: SPRAY
Manufacturer: KROGER COMPANY
Category: otc | Type: HUMAN OTC DRUG LABEL
Date: 20250812

ACTIVE INGREDIENTS: OXYMETAZOLINE HYDROCHLORIDE 0.05 mg/1 mL
INACTIVE INGREDIENTS: BENZALKONIUM CHLORIDE; BENZYL ALCOHOL; CAMPHOR (NATURAL); EDETATE DISODIUM; EUCALYPTOL; GLYCERIN; MENTHOL, UNSPECIFIED FORM; MICROCRYSTALLINE CELLULOSE; CARBOXYMETHYLCELLULOSE SODIUM, UNSPECIFIED; POLYETHYLENE GLYCOL, UNSPECIFIED; POVIDONE, UNSPECIFIED; PROPYLENE GLYCOL; WATER; SODIUM PHOSPHATE, DIBASIC, UNSPECIFIED FORM; SODIUM PHOSPHATE, MONOBASIC, UNSPECIFIED FORM; XANTHAN GUM

Kroger No Drip Allergy Nasal Mist Drug Facts

Active ingredient

Oxymetazoline hydrochloride 0.05%

Purpose

Nasal Decongestant

Uses

- temporarily relieves nasal congestion due to:
- common cold
- hay fever
- upper respiratory allergies
- temporarily relieves sinus congestion and pressure
- shrinks swollen nasal membranes so you can breathe more freely

Ask a doctor before use if you have

- heart disease
- high blood pressure
- thyroid disease
- diabetes
- trouble urinating due to an enlarged prostate gland

When using this product

- do not use more than directed
- do not use for more than 3 days. Use only as directed. Frequent or prolonged use may cause nasal congestion to recur or worsen.
- temporary discomfort such as burning, stinging, sneezing or an increase in nasal discharge may occur
- use of this container by more than one person may spread infection

Stop use and ask a doctor if

symptoms persist

If pregnant or breast-feeding,

ask a health professional before use.

Keep out of reach of children.

If swallowed, get medical help or contact a Poison Control Center right away at (1-800-222-1222).

Directions

- adults and children 6 to under 12 years of age (with adult supervision):2 or 3 sprays in each nostril not more often than every 10 to 12 hours. Do not exceed 2 doses in any 24-hour period.
- children under 6 years of age:ask a doctor

To use:Shake well before use. Push down cap while turning counter-clockwise. Before using the first time, prime metered pump by depressing pump firmly several times. To spray, hold bottle with thumb at base and nozzle between first and second fingers. Without tilting head, insert nozzle into nostril. Fully depress rim with a firm, even stroke and sniff deeply. Wipe nozzle clean after use. Replace clip under rim and secure cap after use.

Other information

- store at room temperature

No Drip

Allergy Sinus

Nasal Mist

Nasal Decongestant

Oxymetazoline HCl

Nasal Solution

PUMP MIST

Kroger® No Drip Nasal Mist is a breakthrough in nasal sprays. It stays where you spray it without messy dripping from your nose or down your throat. It starts to work in seconds providing up to 12 hours of nasal congestion relief without drowsiness.

Up to 12-hours relieffrom nasal congestion. Relief can last All-Dayor All- Night.

Inactive ingredients

benzalkonium chloride, benzyl alcohol, camphor, edetate disodium, eucalyptol, glycerin, menthol, microcrystalline cellulose and carboxymethylcellulose sodium, polyethylene glycol, povidone, propylene glycol, purified water, sodium phosphate dibasic, sodium phosphate monobasic, xanthan gum.

Package/Label Principal Display Panel

COMPARE TO the active ingredient in AFRIN® NO DRIP ALLERGY SINUS*See side panel

NDC# 30142-718-30

NO DRIP

Allergy Sinus

Nasal Mist

Nasal Decongestant

Oxymetazoline HCl

Nasal Solution

Fast, Powerful Congestion Relief from Allergies

Up to 12 Hour Relief

Won’t Drip From Nose or Down Throat

Reduces swelling of Nasal Passages

1 FL OZ (30 mL)

DISTRIBUTED BY: THE KROGER CO.

CINCINNATI, OHIO 45202

For More Product Information, Scan UPC

Using your Kroger App or call 800-632-6900

IMPORTANT: Keep this carton for future reference on full labeling.

* Afrin®No Drip Allergy Sinus is a registered trademark of Bayer Healthcare LLC, Whippany, NJ 07981. Bayer Healthcare LLC is not affiliated with The Kroger Co. or this product.